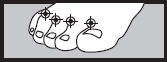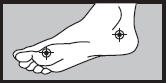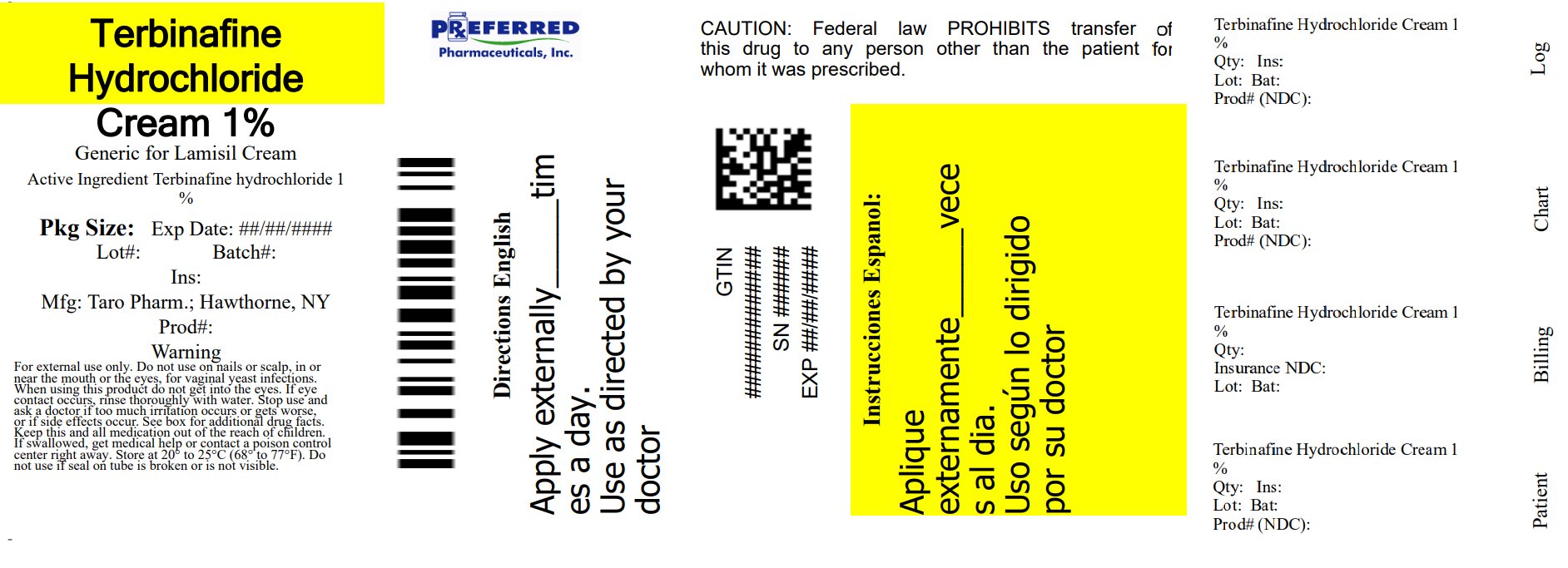 DRUG LABEL: Terbinafine Hydrochloride
NDC: 68788-9814 | Form: CREAM
Manufacturer: Preferred Pharmaceuticals, Inc
Category: otc | Type: HUMAN OTC DRUG LABEL
Date: 20250930

ACTIVE INGREDIENTS: Terbinafine Hydrochloride 1 g/100 g
INACTIVE INGREDIENTS: benzyl alcohol; cetyl alcohol; cetyl palmitate; isopropyl myristate; polysorbate 60; water; sodium hydroxide; sorbitan monostearate; stearyl alcohol

Terbinafine Hydrochloride
Cream 1%
Antifungal Cream

Drug Facts

Active ingredient

Terbinafine hydrochloride 1%

Purpose

Antifungal

Uses

- cures most athlete's foot (tinea pedis)
- cures most jock itch (tinea cruris) and ringworm (tinea corporis)
- relieves itching, burning, cracking and scaling which accompany these conditions

Warnings

For external use only

Do not use

- on nails or scalp
- in or near the mouth or the eyes
- for vaginal yeast infections

When using this product do not get into the eyes. If eye contact occurs, rinse thoroughly with water.

Stop use and ask a doctor if

- too much irritation occurs or gets worse.
- side effects occur. You may report side effects to FDA at 1-800-FDA-1088.

Keep out of reach of children. If swallowed, get medical help or contact a poison control center right away.

Directions

- adults and children 12 years and older
  - use the tip of the cap to break the seal and open the tube
  - wash the affected skin with soap and water and dry completely before applying
  - for athlete's foot wear well-fitting, ventilated shoes. Change shoes and socks at least once daily.
    - between the toes only: apply twice a day (morning and night) for 1 week or as directed by a doctor.
    - on the bottom or sides of the foot: apply twice a day (morning and night) for 2 weeks or as directed by a doctor.
  - for jock itch and ringworm: apply once a day (morning or night) for 1 week or as directed by a doctor.
  - wash hands after each use
- children under 12 years: ask a doctor

1 week between the toes
2 weeks on the bottom or sides of the foot

Other information

- do not use if seal on tube is broken or is not visible
- store at controlled room temperature 20°-25°C (68°-77°F)
- see carton or tube crimp for lot number and expiration date

Inactive ingredients

benzyl alcohol, cetyl alcohol, cetyl palmitate, isopropyl myristate, polysorbate 60, purified water, sodium hydroxide, sorbitan monostearate, stearyl alcohol.

Distributed by:
Taro Pharmaceuticals U.S.A., Inc.
Hawthorne, NY 10532

Relabeled By: Preferred Pharmaceuticals Inc.

PRINCIPAL DISPLAY PANEL - 30 g Carton

Cures Most Athlete's Foot
Terbinafine Hydrochloride
Cream 1%
Antifungal Cream

Full Prescription Strength

NET WT 1 oz (30 g)